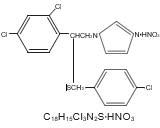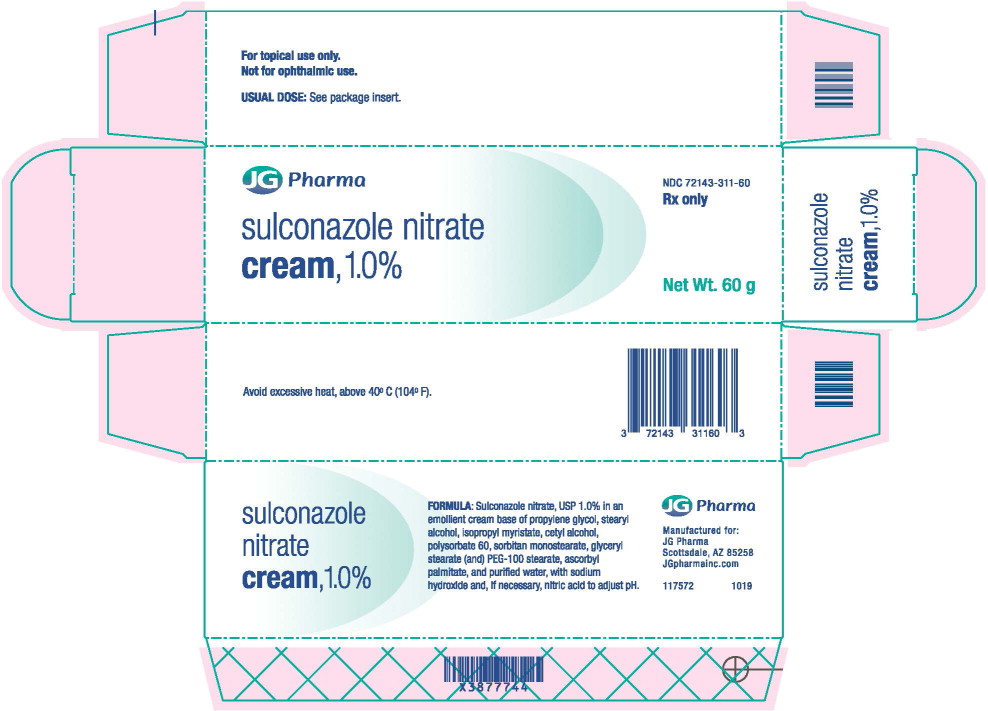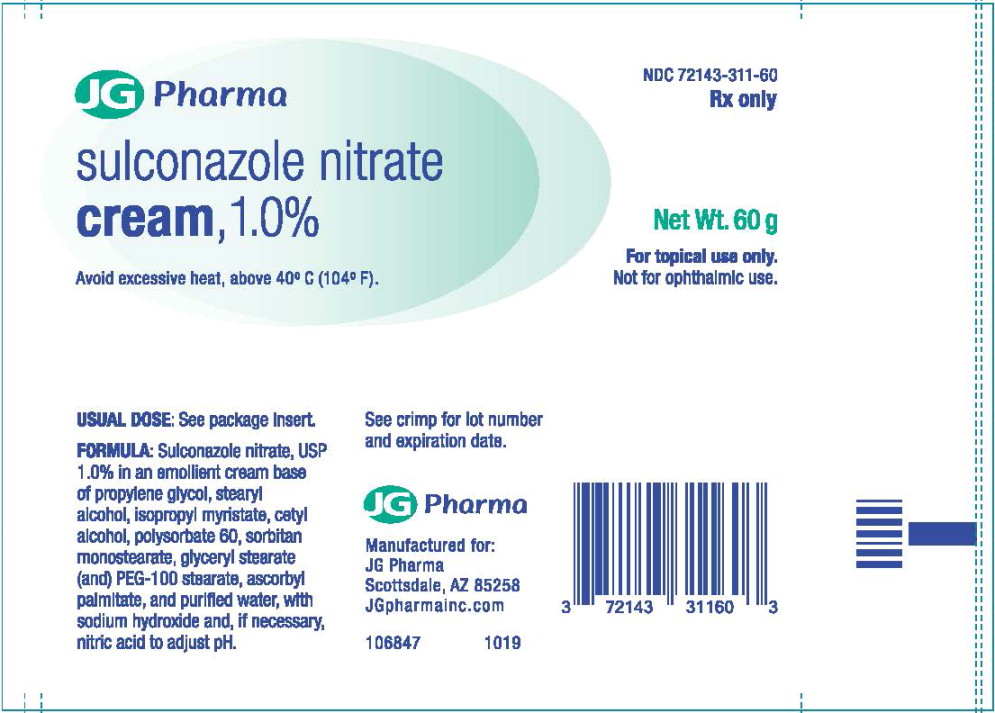 DRUG LABEL: Sulconazole Nitrate
NDC: 72143-311 | Form: CREAM
Manufacturer: JG Pharma
Category: prescription | Type: HUMAN PRESCRIPTION DRUG LABEL
Date: 20241223

ACTIVE INGREDIENTS: SULCONAZOLE NITRATE 10 mg/1 g
INACTIVE INGREDIENTS: PROPYLENE GLYCOL; STEARYL ALCOHOL; ISOPROPYL MYRISTATE; CETYL ALCOHOL; POLYSORBATE 60; SORBITAN MONOSTEARATE; GLYCERYL MONOSTEARATE; PEG-100 STEARATE; ASCORBYL PALMITATE; WATER; SODIUM HYDROXIDE; NITRIC ACID

SULCONAZOLE NITRATE
cream 1.0%

Rx only

For topical use only. Not for ophthalmic use.

DESCRIPTION

SULCONAZOLE NITRATE cream 1.0% is a broad-spectrum antifungal agent intended for topical application. Sulconazole nitrate, USP, the active ingredient in SULCONAZOLE NITRATE cream, is an imidazole derivative with in vitroantifungal and antiyeast activity. Its chemical name is (±)-1-[2,4-Dichloro-β-[(p-chlorobenzyl)thio] phenethyl]imidazole mononitrate and it has the following chemical structure:

Sulconazole nitrate, USP is a white to off-white crystalline powder with a molecular weight of 460.77. It is freely soluble in pyridine; slightly soluble in ethanol, acetone, and chloroform; and very slightly soluble in water. It has a melting point of about 130°C.

SULCONAZOLE NITRATE cream contains sulconazole nitrate, USP 10 mg/g in an emollient cream base consisting of propylene glycol, stearyl alcohol, isopropyl myristate, cetyl alcohol, polysorbate 60, sorbitan monostearate, glyceryl stearate (and) PEG-100 stearate, ascorbyl palmitate, and purified water, with sodium hydroxide and/or nitric acid added to adjust the pH.

CLINICAL PHARMACOLOGY

Sulconazole nitrate is an imidazole derivative with broad-spectrum antifungal activity that inhibits the growth in vitroof the common pathogenic dermatophytes, including Trichophyton rubrum, Trichophyton mentagro- phytes, Epidermophyton floccosumand Microsporum canis. It also inhibits (in vitro) the organism responsible for tinea versicolor, Malassezia furfur. Sulconazole nitrate has been shown to be active in vitroagainst the following microorganisms, although clinical efficacy has not been established: Candida albicansand certain gram-positive bacteria.

A modified Draize test showed no allergic contact dermatitis and a phototoxicity study showed no phototoxic or photoallergic reaction to sulconazole nitrate cream. Maximization tests with sulconazole nitrate cream showed no evidence of contact sensitization or irritation.

INDICATIONS AND USAGE

SULCONAZOLE NITRATE cream 1.0% is an antifungal agent indicated for the treatment of tinea pedis (athlete's foot), tinea cruris, and tinea corporis caused by Trichophyton rubrum, Trichophyton mentagro- phytes, Epidermophyton floccosum, and Microsporum canis,* and for the treatment of tinea versicolor.

CONTRAINDICATIONS

SULCONAZOLE NITRATE cream 1.0% is contraindicated in patients who have a history of hypersensitivity to any of its ingredients.

PRECAUTIONS

General

SULCONAZOLE NITRATE cream 1.0% is for external use only. Avoid contact with the eyes. If irritation develops, the cream should be discontinued and appropriate therapy instituted.

Information for Patients

Patients should be told to use SULCONAZOLE NITRATE cream as directed by the physician, to use it externally only, and to avoid contact with the eyes.

Carcinogenesis, Mutagenesis, Impairment of Fertility

Long-term animal studies to determine carcinogenic potential have not been performed. In vitrostudies have shown no mutagenic activity.

Pregnancy

There are no adequate and well-controlled studies in pregnant women. Sulconazole nitrate should be used during pregnancy only if clearly needed. Sulconazole nitrate has been shown to be embryotoxic in rats when given in doses of 125 times the adult human dose (in mg/kg). The drug was not teratogenic in rats or rabbits at oral doses of 50 mg/kg/day.

Sulconazole nitrate given orally to rats at a dose 125 times the human dose resulted in prolonged gestation and dystocia. Several females died during the prenatal period, most likely due to labor complications.

Nursing Mothers

It is not known whether sulconazole nitrate is excreted in human milk. Caution should be exercised when sul- conazole nitrate is administered to a nursing woman.

*Efficacy for this organism in the organ system was studied in fewer than 10 infections.

Pediatric Use

Safety and effectiveness in children have not been established.

Geriatric Use

Clinical studies of SULCONAZOLE NITRATE cream 1.0%, did not include sufficient numbers of patients aged 65 years and over to determine whether they respond differently than younger patients. Other reported clinical experience has not identified differences in responses between elderly and younger patients.

ADVERSE REACTIONS

There were no systemic effects and only infrequent cutaneous adverse reactions in 1185 patients treated with sulconazole nitrate cream in controlled clinical trials. Approximately 3% of these patients reported itching, 3% burning or stinging, and 1% redness. These complaints did not usually interfere with treatment.

CLINICAL STUDIES

In a vehicle-controlled study for the treatment of tinea pedis (moccasin type) due to T. rubrum, after 4 to 6 weeks of treatment 69% of patients on the active drug and 19% of patients on the drug vehicle had become KOH- and culture-negative. In addition, 68% of patients on the active drug and 20% of patients on the drug vehicle showed a good or excellent clinical response.

DOSAGE AND ADMINISTRATION

A small amount of cream should be gently massaged into the affected and surrounding skin areas once or twice daily, except in tinea pedis, where administration should be twice daily.

Early relief of symptoms is experienced by the majority of patients and clinical improvement may be seen fairly soon after treatment is begun; however, tinea corporis/cruris and tinea versicolor should be treated for 3 weeks and tinea pedis for 4 weeks to reduce the possibility of recurrence.

If significant clinical improvement is not seen after 4 to 6 weeks of treatment, an alternate diagnosis should be considered.

HOW SUPPLIED

SULCONAZOLE NITRATE cream 1.0% is a smooth, glossy white to off-white cream having a slight characteristic odor. It is supplied as follows:

60 g tube - NDC 72143-311-60

Avoid excessive heat, above 40° C (104° F).

To report SUSPECTED ADVERSE REACTIONS, contact the FDA at 1-800-FDA-1088 or www.fda.gov/medwatch.

Manufactured for:
JG Pharma
Scottsdale, AZ
85258
www.JGPharmainc.com

141079
September 2019

Principal Display Panel – 60g Carton Label

JG Pharma

NDC 72143-311-60

Rx only

sulconazole nitrate
cream, 1.0%

Net Wt. 60 g

Principal Display Panel – 60g Tube Label

JG Pharma

NDC 72143-311-60

Rx only

sulconazole nitrate
cream, 1.0%

Avoid excessive heat, above 40°C (104° F).

Net Wt. 60 g

For topical use only.

Not for ophthalmic use.